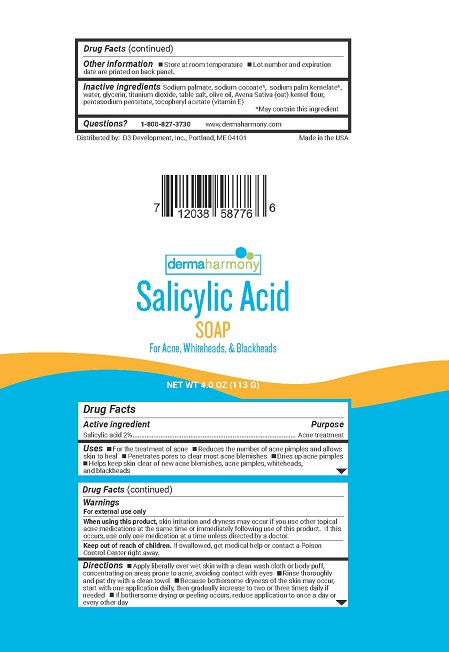 DRUG LABEL: Salicylic Acid
NDC: 71819-003 | Form: SOAP
Manufacturer: D3 Development, Inc.
Category: otc | Type: HUMAN OTC DRUG LABEL
Date: 20180504

ACTIVE INGREDIENTS: SALICYLIC ACID 2 g/100 g
INACTIVE INGREDIENTS: SODIUM CHLORIDE; TITANIUM DIOXIDE; WATER; SODIUM COCOATE; GLYCERIN; OATMEAL; SODIUM PALM KERNELATE; OLIVE OIL; SODIUM PALMATE; .ALPHA.-TOCOPHEROL ACETATE, D-; PENTASODIUM PENTETATE

Dermaharmony Salicylic Acid Soap

Drug Facts

Active ingredient

Salicylic acid 2%

Purpose

Acne treatment

Uses

- For the treatment of acne
- Reduces the number of acne pimples and allows skin to heal
- Penetrates pores to clear most acne blemishes
- Dries up acne pimples
- Helps keep skin clear of new acne blemishes, acne pimples, whiteheads, and blackheads

Warnings

For external use only

When using this product, skin irritation and dryness may occur if you use other topical acne medications at the same time or immediately following use of this product. If this occurs, use only one medication at a time unless directed by a doctor.

Keep out of reach of children. If swallowed, get medical help or contact a Poison Control Center right away.

Directions

- Apply liberally over wet skin with a clean wash cloth or body puff, concentrating on areas prone to acne, avoiding contact with eyes.
- Rinse thoroughly and pat dry with a clean towel
- Because bothersome dryness of the skin may occur, start with one application daily, then gradually increase to two or three times daily if needed
- if bothersome dryness or peeling occurs, reduce application to once a day or every other day

Other information

- Store at room temperature
- Lot number and expiration date are printed on back panel.

Inactive ingredients

Sodium palmate, sodium cocoate*, sodium palm kernelate*, water, glycerin, titanium dioxide, table salt, olive oil, Avena Sativa (oat) kernel flour, pentasodium pentetate, tocopheryl acetate (vitamin E)

Questions?

1-800-827-3730

www.dermaharmony.com

Distributed by:

D3 Development, Inc., Portland, ME 04101

Made in the USA

PACKAGE LABEL

dermaharmony

Salicylic Acid SOAP

For Acne, Whiteheads, & Blackheads

NET WT 4.0 OZ (113 G)